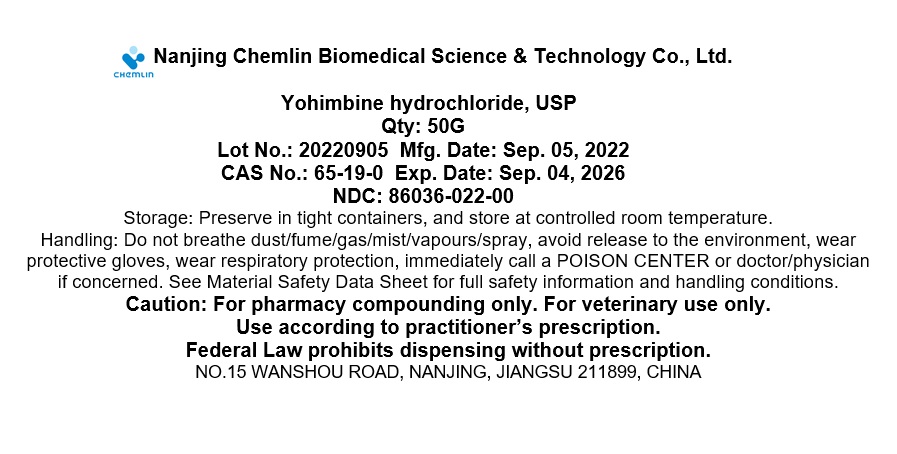 DRUG LABEL: Yohimbine HCl
NDC: 86036-022 | Form: POWDER
Manufacturer: Nanjing Chemlin Biomedical Science & Technology Co, Ltd.
Category: other | Type: BULK INGREDIENT - ANIMAL DRUG
Date: 20240823

ACTIVE INGREDIENTS: YOHIMBINE HYDROCHLORIDE 1 g/1 g

Yohimbine HCl